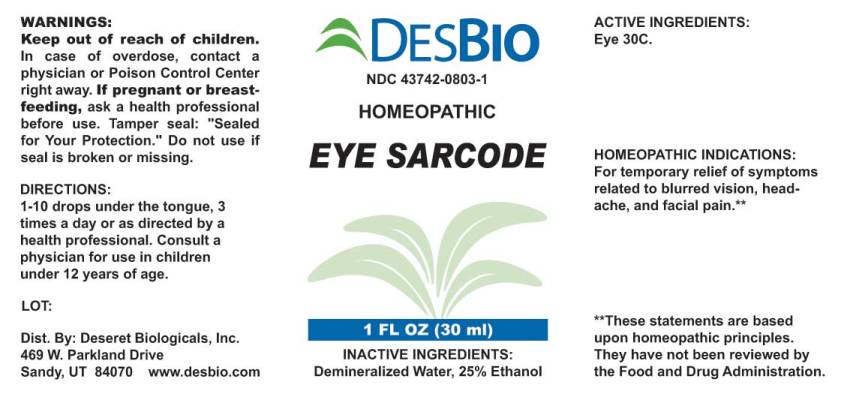 DRUG LABEL: Eye Sarcode
NDC: 43742-0803 | Form: LIQUID
Manufacturer: Deseret Biologicals, Inc.
Category: homeopathic | Type: HUMAN OTC DRUG LABEL
Date: 20230509

ACTIVE INGREDIENTS: SUS SCROFA EYE 30 [hp_C]/1 mL
INACTIVE INGREDIENTS: WATER; ALCOHOL

Drug Facts:

ACTIVE INGREDIENTS:

Eye (Suis) 30C.

HOMEOPATHIC INDICATIONS:

For temporary relief of symptoms related to blurred vision, headache, and facial pain.**

**These statements are based upon traditional homeopathic principles. They have not been reviewed by the Food and Drug Administration.

WARNINGS:

Keep out of reach of children. In case of overdose, contact physician or a Poison Control Center right away.

If pregnant or breast-feeding, ask a health professional before use.

Tamper seal: "Sealed for Your Protection." Do not use if seal is broken or missing.

Keep out of reach of children. In case of overdose, contact physician or a Poison Control Center right away.

DIRECTIONS:

1-10 drops under the tongue, 3 times a day or as directed by a health professional. Consult a physician for use in children under 12 years of age.

HOMEOPATHIC INDICATIONS:

For temporary relief of symptoms related to blurred vision, headache, and facial pain.**

**These statements are based upon traditional homeopathic principles. They have not been reviewed by the Food and Drug Administration.

INACTIVE INGREDIENTS:

Demineralized Water, 25% Ethanol

QUESTIONS:

Dist. By: Deseret Biologicals, Inc.
469 W. Parkland Drive
Sandy, UT 84070 www.desbio.com

PACKAGE LABEL DISPLAY:

DESBIO

NDC 43742-0803-1

HOMEOPATHIC

EYE SARCODE

1 FL OZ (30 ml)